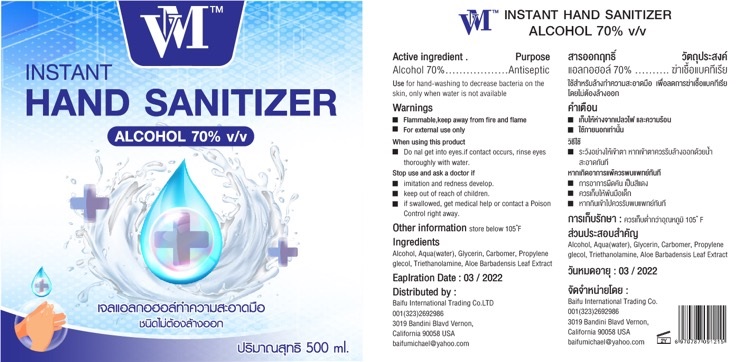 DRUG LABEL: VM Instant HAND SANITIZER
NDC: 77681-006 | Form: GEL
Manufacturer: BEAUTY NATURAL INTER COMPANY LIMITED
Category: otc | Type: HUMAN OTC DRUG LABEL
Date: 20200513

ACTIVE INGREDIENTS: ALCOHOL 70 mL/100 mL
INACTIVE INGREDIENTS: WATER; TROLAMINE; PROPYLENE GLYCOL; ALOE VERA LEAF; GLYCERIN

HAND SANITIZER

Active ingredient

Alcohol 70%

Purpose

Antiseptic

Use

For hand-washing to decrease bacteria on skin, only when water is not available.

Warnings

For external use only.

Flammable.Keep product away from fire or flame.

When using this product

Do not get into eyes, if contact occurs rinse eyes thoroughly with water.

Stop use and ask a doctor if

irritation or redness develops.

Keep out of reach of children.

If swallowed, get medical help or contact a Poison Control Center right away.

Directions

Place enough product on your palm to thoroughly cover your hads. Rub hands together briskly until dry. Children under 6 years of age should be supervised when using this product.

Inactive ingredients

Aqua (water), Glycerin, Carbomer, Propylene Glecol, TRIETHANOLAMINE, Aloe Barbadensis Leaf Extract

Other information:

Store below 105℉